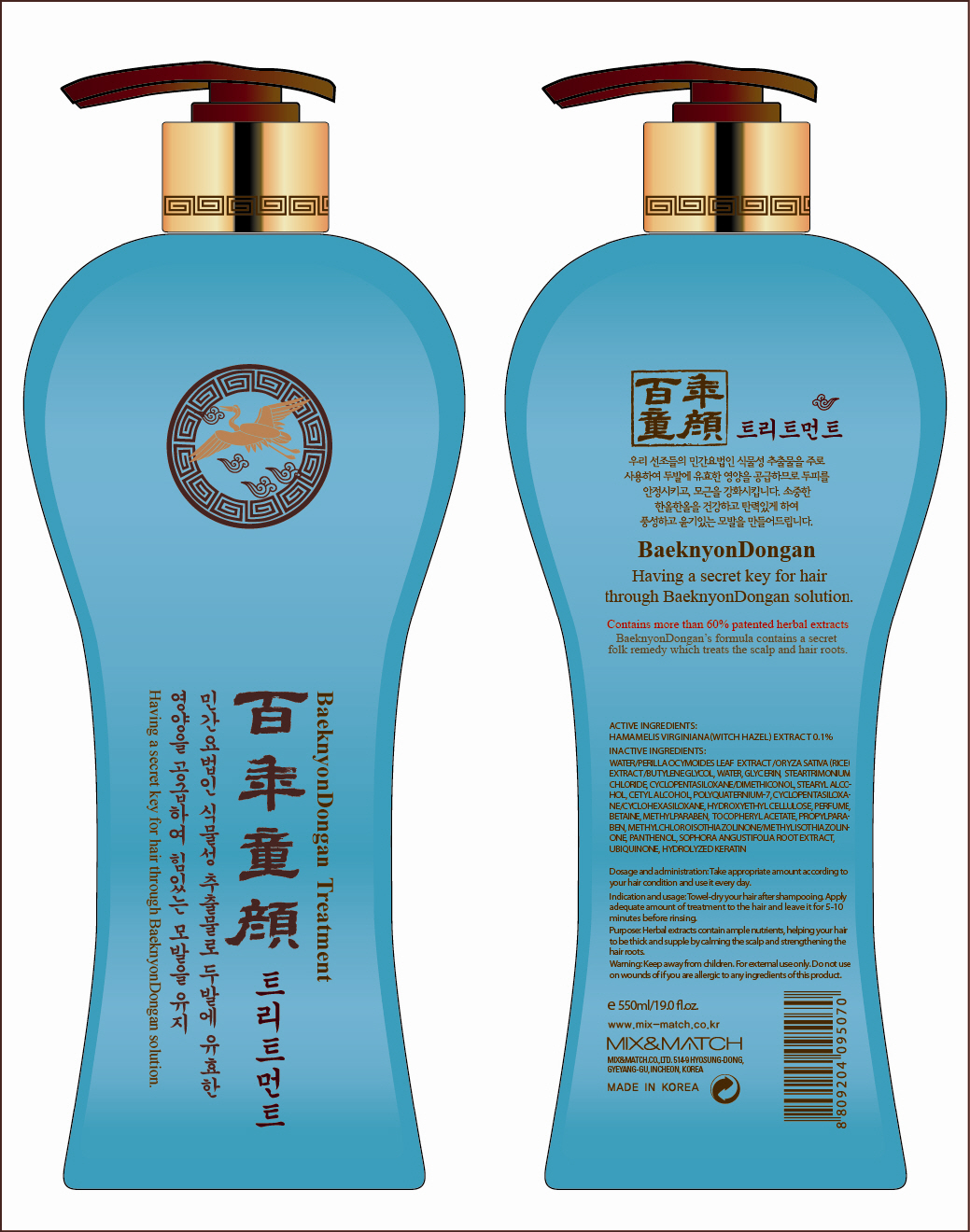 DRUG LABEL: BAEKNYONDONGAN TREATMENT
NDC: 54948-100 | Form: SOLUTION
Manufacturer: MIX & MATCH CO., LTD.
Category: otc | Type: HUMAN OTC DRUG LABEL
Date: 20120530

ACTIVE INGREDIENTS: WITCH HAZEL 0.55 mL/550 mL
INACTIVE INGREDIENTS: WATER; PERILLA FRUTESCENS LEAF; BUTYLENE GLYCOL; GLYCERIN; TRIMETHYL OCTADECYL AMMONIUM CHLORIDE; CYCLOMETHICONE 5; STEARYL ALCOHOL; CETYL ALCOHOL; CYCLOMETHICONE 6; BETAINE; METHYLPARABEN; PROPYLPARABEN; PANTHENOL; SOPHORA FLAVESCENS ROOT

Drug Facts

Active ingredient: WITCH HAZEL 0.1%

Inactive ingredients:
Water, Perilla Ocymoides Leaf Extract, Oryza Sativa (Rice) Extract, Butylene Glycol, Glycerin, Steartrimonium Chloride, Cyclopentasiloxane, Dimethiconol, Stearyl Alcohol, Cetyl Alcohol, Polyquaternium-7, Cyclohexasiloxane, Hydroxyethyl cellulose, Perfume, Betaine, Methylparaben, Tocopheryl Acetate, Propylparaben, Methylchloroisothiazolinone, Methylisothiazolinone, Panthenol, Sophora Angustifolia Root Extract, Ubiquinone, Hydrolyzed keratin

Purpose: Skin Protectant

Warnings:
For external use only.
Do not use on wounds of if you are allergic to any ingredients of this product.

Keep out of reach of children:
Keep away from children.

Indication and usage:
Towel dry your hair after shampooing.
Apply adequate amount of treatment to the hair and leave it for 5-10 minutes before rinsing.

Dosage and administration:
Take appropriate amount according to your hair condition and use it every day.